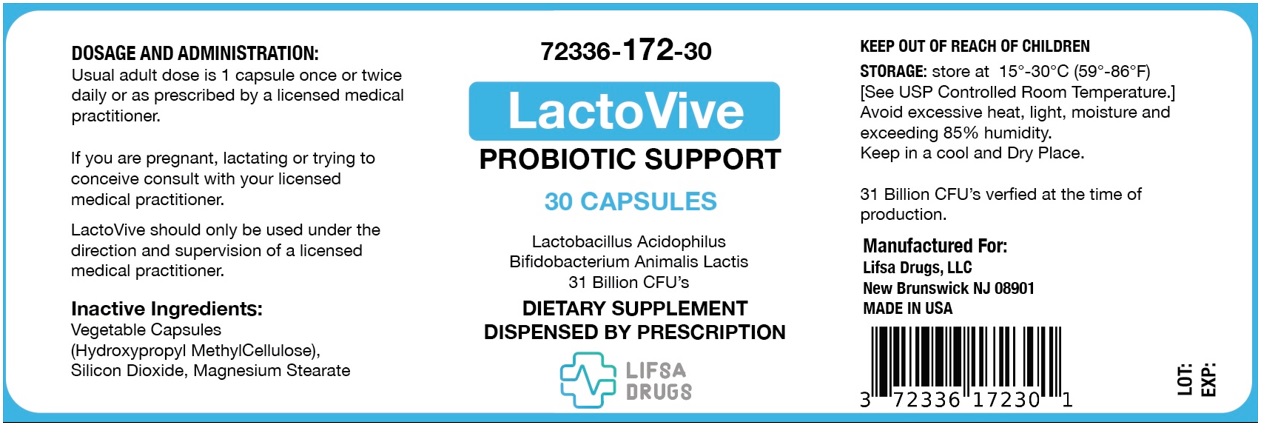 DRUG LABEL: LactoVive
NDC: 72336-172 | Form: CAPSULE
Manufacturer: Lifsa Drugs LLC
Category: other | Type: DIETARY SUPPLEMENT
Date: 20250318

ACTIVE INGREDIENTS: LACTOBACILLUS ACIDOPHILUS 16000000000 [CFU]/1 1; BIFIDOBACTERIUM ANIMALIS LACTIS 15000000000 [CFU]/1 1
INACTIVE INGREDIENTS: HYPROMELLOSE, UNSPECIFIED; SILICON DIOXIDE; MAGNESIUM STEARATE

LactoVive

HEALTH CLAIM

72336-172-30

PROBIOTIC SUPPORT

DIETARY SUPPLEMENT

DISPENSED BY PRESCRIPTION

DESCRIPTION

LactoVive is an orally administered prescription probiotic dietary supplement.

STATEMENT OF IDENTITY

Supplement Facts
Serving size 1 Capsule
Amount per Serving: |  | % Daily Value
Lactobacillus Acidophilus | 16 Billion | [Daily value not established]
Bifidobacterium Animalis Lactis | 15 Billion

Inactive Ingredients:

Vegetable Capsules

Hydroxypropyl Methylcellulose, Silicon Dioxide, Magnesium Stearate.

Preservative Free and Gluten Free

INDICATIONS

LactoVive is an orally administered prescription probiotic formulation for the clinical dietary management of suboptimal nutritional status in patients where advanced supplementation is required and nutritional supplementation in physiologically stressful conditions for maintenance of good health is needed. LactoVive should be administered under the supervision of a licensed medical practitioner.

CONTRAINDICATIONS

This product is contraindicated in patients with a known hypersensitivity to any of the ingredients.

WARNING

LactoVive should only be used under the direction and supervision of a licensed medical practitioner. Use with caution in patients that may have a medical condition, are pregnant, lactating, trying to conceive, under the age of 18, or taking other medications.

ADVERSE REACTIONS

You should call your doctor for medical advice about serious adverse events. To report adverse side effects or to obtain product information, contact Lifsa Drugs, LLC at 1-800-FDA-1088

DOSAGE AND ADMINISTRATION

Usual adult dose is 1 capsule once or twice daily or as prescribed by a licensed medical practitioner.

HOW SUPPLIED

Bottle of 30 capsules (72336-172-30)

STORAGE AND HANDLING

Store 15°-30°C (59°-86°F) [See USP Controlled Room Temperature.] Avoid excessive heat, light, moisture and exceeding 85% humidity. Keep in a cool, dry place.

TAMPER EVIDENT: Do not use if seal is broken or missing.

HEALTH CLAIM

31 Billion CFU's verified at the time of production.

Manufactured For:

Lifsa Drugs, LLC

New Brunswick NJ 08901

MADE IN USA

These statements have not been evaluated by the Food and Drug Administration. This product is not intended to diagnose, treat, cure, or prevent any diseases.

KEEP THIS AND ALL MEDICATIONS OUT OF THE REACH OF CHILDREN

PRINCIPAL DISPLAY PANEL - 30 Capsule Bottle Label

72336-172-30

Lactobacillus Acidophilus
Bifidobacterium Animalis Lactis
31 Billion CFU's
30 CAPSULES